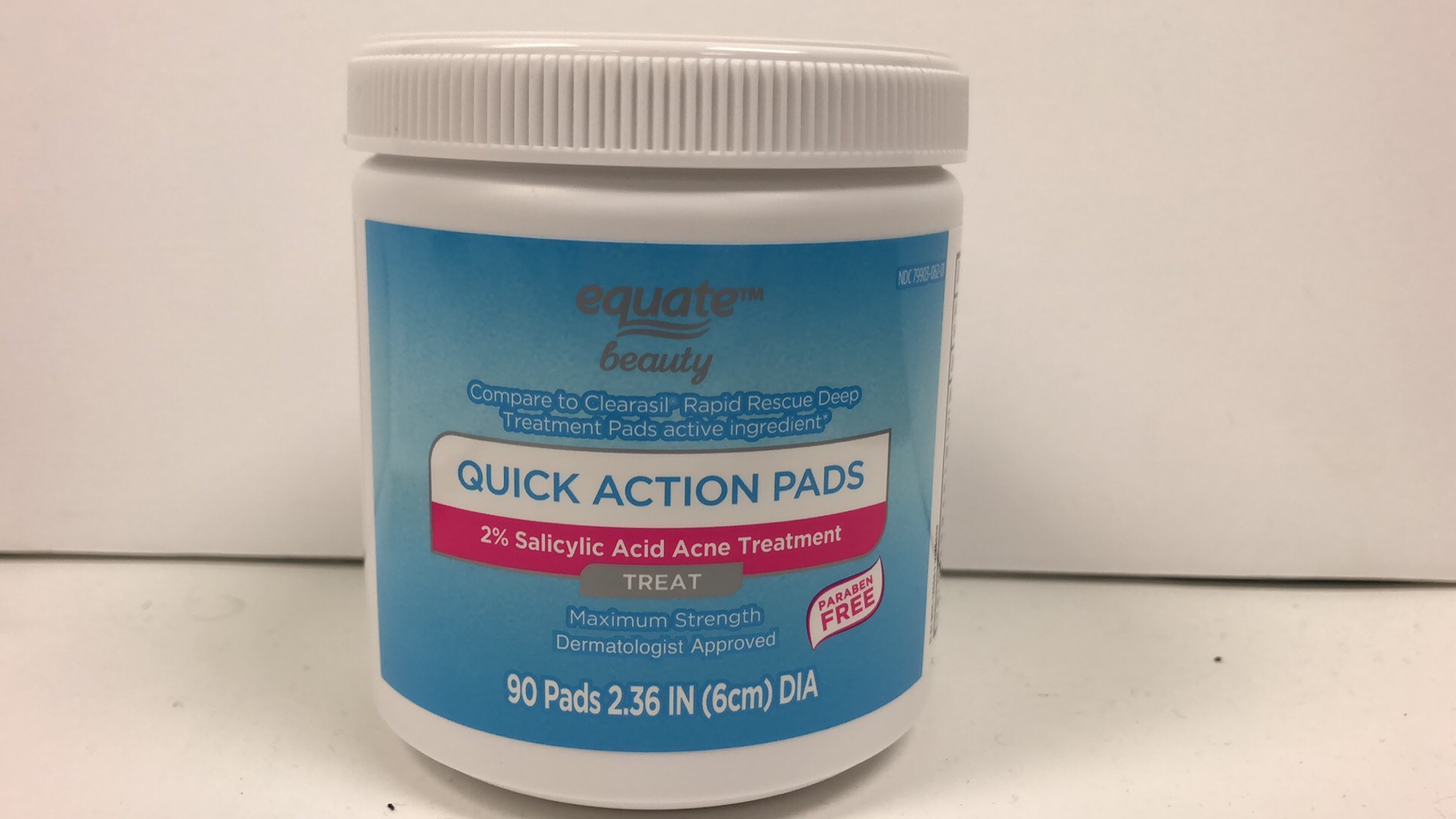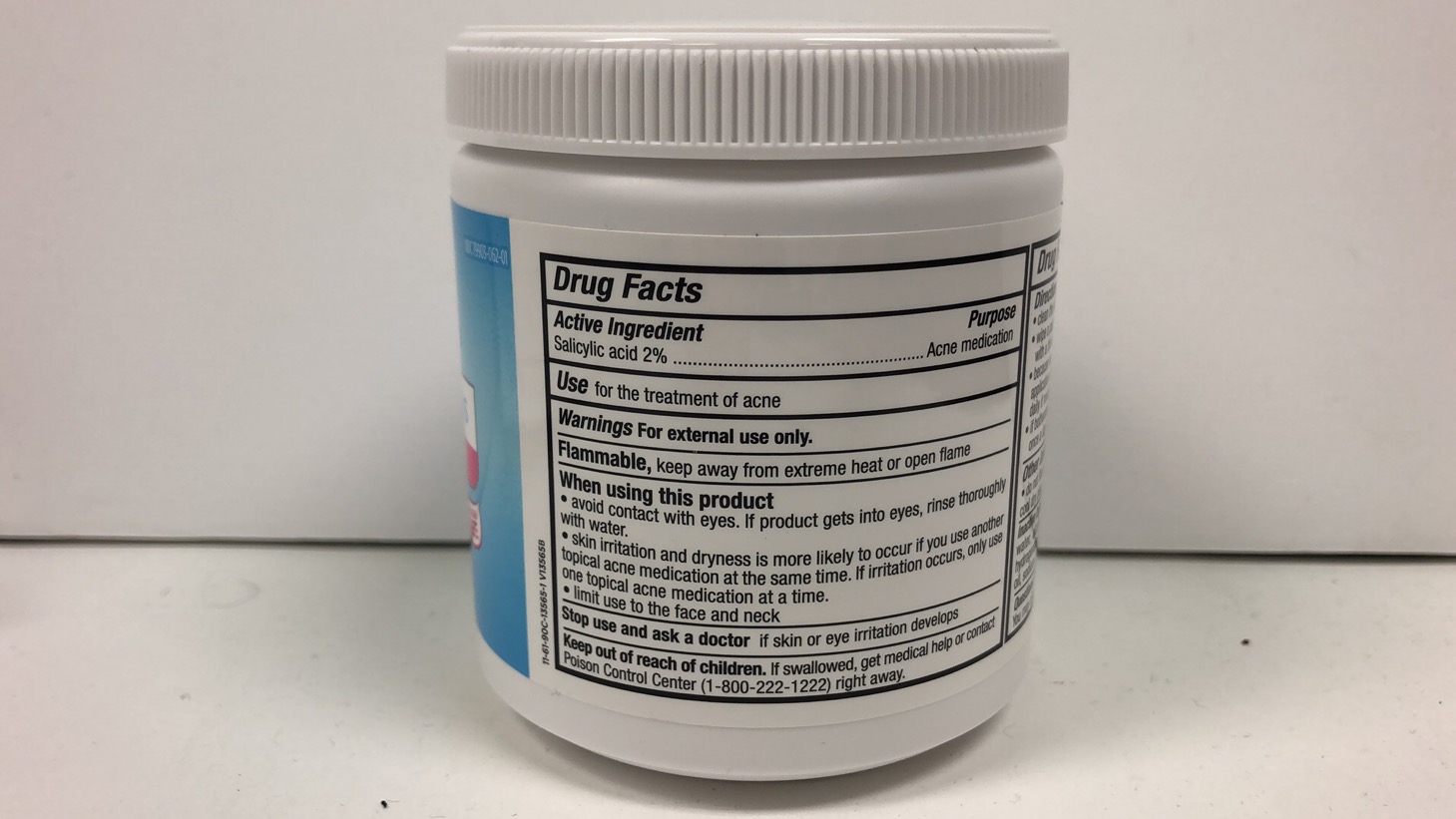 DRUG LABEL: Equate 2% Salicylic acid Acne treatment pad
NDC: 79903-062 | Form: SWAB
Manufacturer: Walmart, Inc.
Category: otc | Type: HUMAN OTC DRUG LABEL
Date: 20260119

ACTIVE INGREDIENTS: SALICYLIC ACID 2 g/100 g
INACTIVE INGREDIENTS: WATER 59.58 g/100 g

Equate -2% Salicylic Acid Quick Action Pad

ACTIVE INGREDIENT

Salicylic acid 2%

WARNINGS

For external use only

PURPOSE

Acne medication

WHEN USING

- avoid contact with the eyes. If product gets into the eyes rinse thoroughly with water.
- skin irritation and dryness is more likely to occur if you use another topical acne medication at the same time. If irritation occurs, only use one topical acne medication at a time.
- limit use to the face and neck

Keep out of reach of children. If swallowed, get medical help or contact Poison Control Center (1-800-222-1222) right away.

Stop use and ask a doctor if skin or eye irritation develops.

OTHER SAFETY INFORMATION

- do not flush in toilet
- keep jar lid tightly closed
- store in cool dry place
- do not freeze

INDICATIONS AND USAGE

Use for the treatment of acne

QUESTIONS

Question? 1-888-287-1915

You may also report side effecs to this phone number.

Directions

- Clean the skin thorougly before applying this product
- wipe a pad over the face and neck to cover the entire affected area with a thin layer one to three times daily
- because excessive drying of the skinmay occur, start with oneapplication daily, then gradually increase to two or three times daily if needed or as directd by a doctor.
- if bothersome dryness or peelingoccur, reduce application to once a day or every other day

INACTIVE INGREDIENT

water, alcohol denat, dipropylene glycol, glycerin, PEG-40 dydrogenated castor oil, sorbitol,fragrance,lavandula angustifolia oil, sodium hydroxide, rose flower oil, disodium EDTA